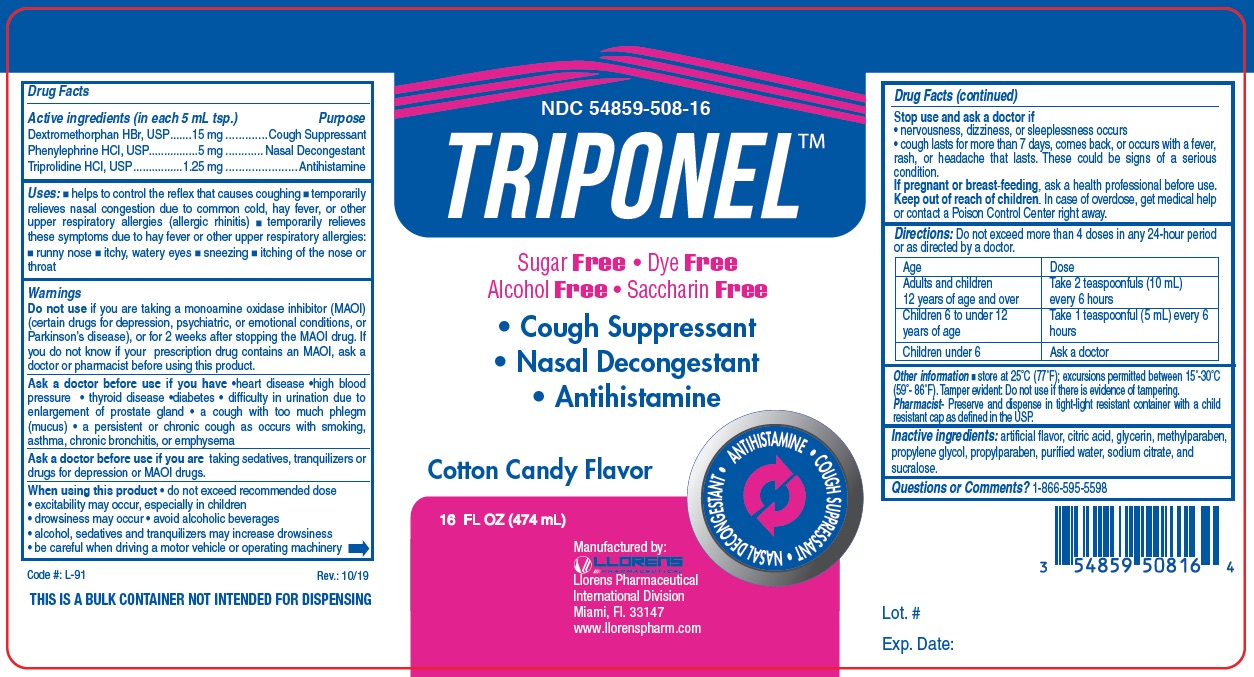 DRUG LABEL: Triponel
NDC: 54859-508 | Form: LIQUID
Manufacturer: LLORENS PHARMACEUTICALS INTERNATIONAL DIVISION
Category: otc | Type: HUMAN OTC DRUG LABEL
Date: 20251231

ACTIVE INGREDIENTS: DEXTROMETHORPHAN HYDROBROMIDE 15 mg/5 mL; PHENYLEPHRINE HYDROCHLORIDE 5 mg/5 mL; TRIPROLIDINE HYDROCHLORIDE 1.25 mg/5 mL
INACTIVE INGREDIENTS: ANHYDROUS CITRIC ACID; GLYCERIN; METHYLPARABEN; PROPYLENE GLYCOL; PROPYLPARABEN; WATER; SODIUM CITRATE; SUCRALOSE

Llorens-Triponel 508

Active Ingredients (in each 5 mL)

Dextromethorphan HBr 15 mg

Phenylephrine HCl 5 mg

Triprolidine HCl 1.25 mg

Purpose

Cough Suppressant

Nasal Decongestant

Antihistamine

Uses

- helps to control the reflex that causes coughing
- temporarily relieves nasal congestion due to common cold, hay fever, or other upper respiratory allergies (allergic, rhinitis)
- temporarily relieves these symptomes due to hay fever or ther upper respiratory allergies
- runny nose
- itchy, watery eyes
- sneexing
- itching of the nose or throat

Warnings

Do not use if you are taking a monoamine oxidase inhibitor (MAOI) (certain drugs for depression, psychiatric, or emotional conditions, or Parkinson's disease), or for 2 weeks after stopping the MAOI drug. If you do not know if you r prescirption drug contains an MAOI, ask a doctor or pharmacist before using this product.

Ask a doctor before use if you have

- heart disease
- high blood pressure
- thyroid disease
- diabetes
- difficulty in urination due to enlargement of prostate gland
- a cough with too much phlegm (mucus)
- a persistent or chronic cough as occurs with smoking, asthma, chronic bronchitis, or emphysema

Ask a doctor before use if you are taking sedatives, tranquilizers or drugs for depression or MAOI drugs.

When using this product

- do not exceed recommended dose
- excitability may occur, especially in children
- drowsiness may occur
- avoid alcoholic beverages
- alcohol, sedatives and tranquilizers may increase drowsiness
- be careful when driving a motor vehicle or operating machinery

Stop use and ask a doctor if

- nervousness dizziness, or sleeplessness occurs
- cough lasts for more than 7 days, comes back, or occurs with a beer, rash, or headache that lasts. These could be signs of a serious condition.

PREGNANCY OR BREAST FEEDING

If pregnant or breast-feeding, ask a health professional before use.

Keep out of reach of children. In case of overdose, get medical help or contact a Poison Control Center right away.

DOSAGE AND ADMINISTRATION

Direcations: Do not exceed more than 4 doses in any 24-hour period or as directed by a doctor.

Age | Dose
Adults and children 12 years of age and over | Take 2 teaspoonfuls (10 mL) every 6 hours
Children 6 to under 12 years of age | Take 1 teaspoonful (5 mL) every 6 hours
Children under 6 | Ask a docotor

INACTIVE INGREDIENT

Inactive ingredients: artificial flavor, citric acid, glycerin, methylparaben, propylene glycol, propylparaben, purified water, sodium citrate, and sucralose.

Questions or Comments? 1-866-595-5598